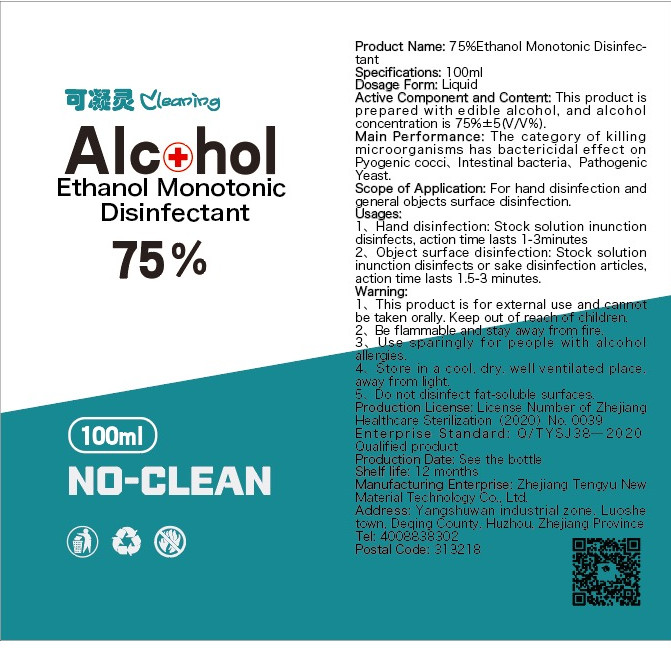 DRUG LABEL: Ethanol Monotonic Disinfectant
NDC: 54983-001 | Form: LIQUID
Manufacturer: Zhejiang Tengyu New Material Technology Co., Ltd.
Category: otc | Type: HUMAN OTC DRUG LABEL
Date: 20200411

ACTIVE INGREDIENTS: ALCOHOL 75 mL/100 mL
INACTIVE INGREDIENTS: WATER

DOSAGE AND ADMINISTRATION

Store in a cool. dry. well ventilated place,away from light.

INACTIVE INGREDIENT

Pure Water

INDICATIONS AND USAGE

1、Hand disinfection: Stock solution inunction disinfects, action time lasts 1-3minutes
2、Object surface disinfection: Stock solution inunction disinfects or sake disinfection articles,action time lasts 1.5-3 minutes.

ACTIVE INGREDIENT

Ethyl alcohol

keep out of children

PURPOSE

Disinfection
Sterilization

WARNINGS

1、This product is for external use and cannot be taken orally. Keep out of reach of children.
2、Be flammable andl stay away from fire.
3、Use sparingly for people with alcohol
allergies.
4 、Store in a cool. dry. well ventilated place.away from light.
5、Do not dlisinfect fat-soluble surfaces.